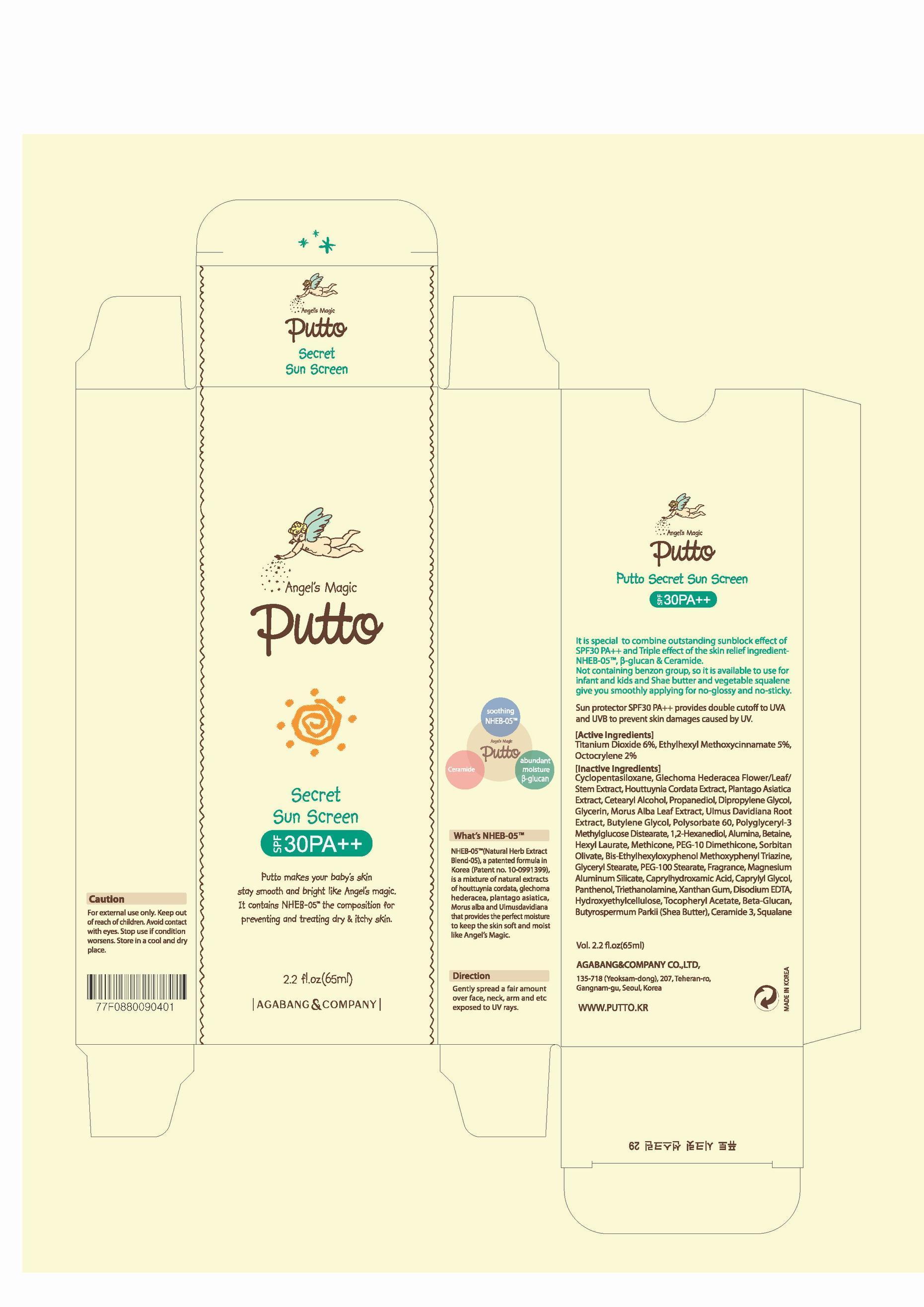 DRUG LABEL: Putto Secret Sun Screen
NDC: 75885-020 | Form: CREAM
Manufacturer: AGABANG & COMPANY 
Category: otc | Type: HUMAN OTC DRUG LABEL
Date: 20130713

ACTIVE INGREDIENTS: TITANIUM DIOXIDE 6 mg/100 mL
INACTIVE INGREDIENTS: CYCLOMETHICONE 5; GLECHOMA HEDERACEA FLOWERING TOP; HOUTTUYNIA CORDATA FLOWERING TOP; PLANTAGO ASIATICA; CETOSTEARYL ALCOHOL; OCTINOXATE; PROPANEDIOL; DIPROPYLENE GLYCOL; GLYCERIN; MORUS ALBA LEAF; ULMUS DAVIDIANA ROOT; POLYSORBATE 60; OCTOCRYLENE

Drug Facts

ACTIVE INGREDIENT

titanium dioxide

INACTIVE INGREDIENT

Cyclopentasiloxane, Glechoma Hederacea Flower/Leaf/Stem Extract, Houttuynia Cordata Extract, Plantago Asiatica Extract, Cetearyl Alcohol, Ethylhexyl Methoxycinnamate, Propanediol, Dipropylene Glycol, Glycerin, Morus Alba Leaf Extract, Ulmus Davidiana Root Extract, Butylene Glycol, Octocrylene, Polysorbate 60, Polyglyceryl-3 Methylglucose Distearate, 1,2-Hexanediol, Alumina, Betaine, Hexyl Laurate, Methicone, PEG-10 Dimethicone, Sorbitan Olivate, Bis-Ethylhexyloxyphenol Methoxyphenyl Triazine, Glyceryl Stearate, PEG-100 Stearate, Fragrance, Magnesium Aluminum Silicate, Caprylhydroxamic Acid, Caprylyl Glycol, Panthenol, Triethanolamine, Xanthan Gum, Disodium EDTA, Hydroxyethylcellulose, Tocopheryl Acetate, Beta-Glucan, Butyrospermum Parkii (Shea Butter), Ceramide 3, Squalane

PURPOSE

sun screen

keep out of reach of the children

INDICATIONS AND USAGE

gently spread a fair amount over face, neck, arm and etc esposed to UV rays

WARNINGS

do not apply to sensitive skin
store in a cool, dry place

DOSAGE AND ADMINISTRATION

for external use only